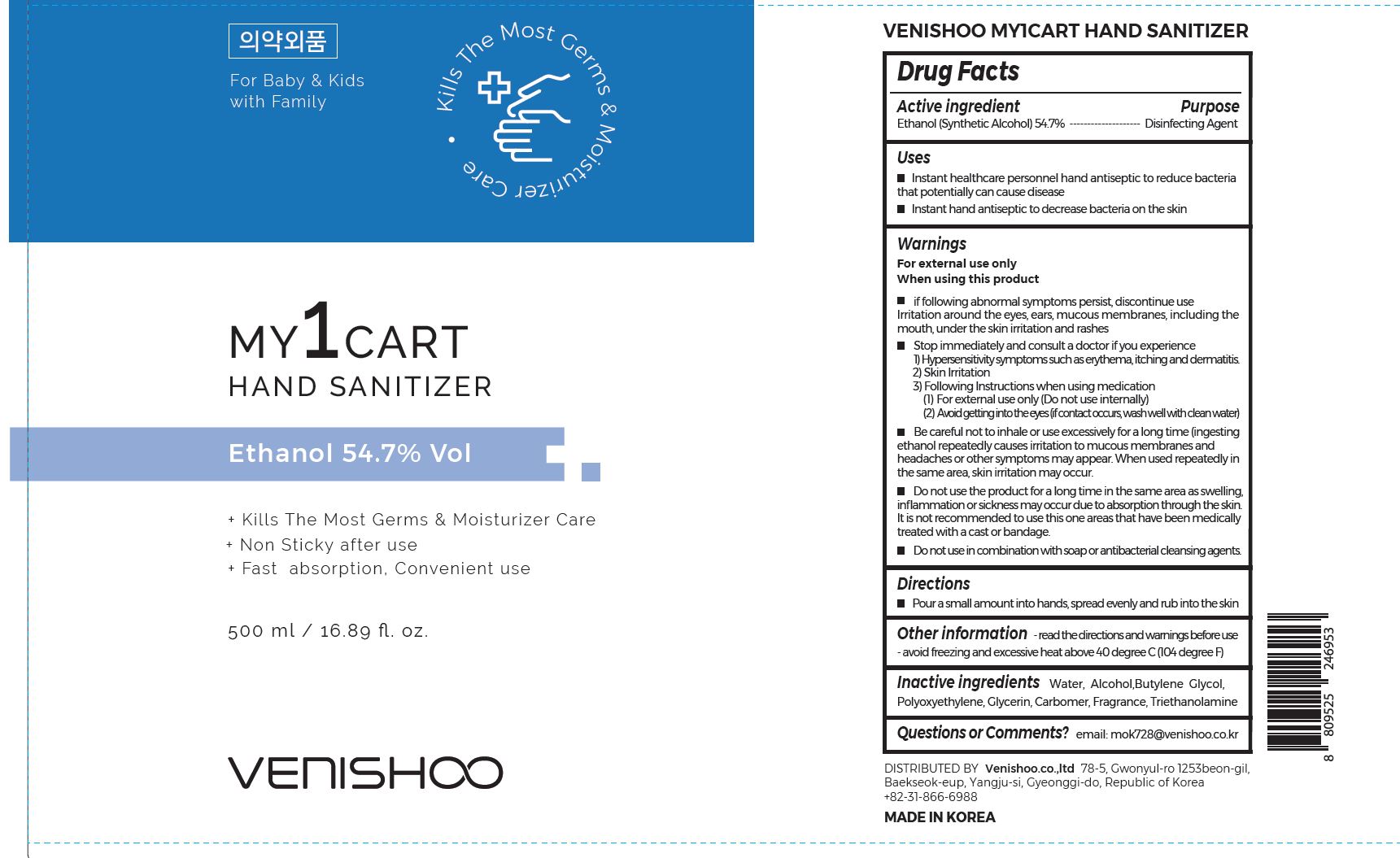 DRUG LABEL: VENISHOO MY1CART HAND SANITIZER
NDC: 78075-0002 | Form: LIQUID, EXTENDED RELEASE
Manufacturer: VENISHOO Co.,Ltd
Category: otc | Type: HUMAN OTC DRUG LABEL
Date: 20200914

ACTIVE INGREDIENTS: ALCOHOL 54.7 mL/100 mL
INACTIVE INGREDIENTS: GLYCERIN; WATER; TROLAMINE; BUTYLENE GLYCOL

Drug Facts

ACTIVE INGREDIENT

ethanol

PURPOSE

■ sterilization of hands and skin

KEEP OUT OF REACH OF THE CHILDREN

WARNINGS

■ Flammable. Keep away from fire or flame.

■ For external use only.

■ Do not use in eyes.

■ lf swallowed, get medical help promptly.

■ Stop use, ask doctor lf irritation occurs.

■ Keep out of reach of children.

DOSAGE AND ADMINISTRATION

for external use only

INACTIVE INGREDIENT

Water, Alcohol,Butylene Glycol,
Polyoxyethylene, Glycerin, Carbomer, Fragrance, Triethanolamine

INDICATIONS AND USAGE

wet hands thoroughly with product and allow to dry without wiping

for children under 6, use only under adult supervision

not recommended for infants